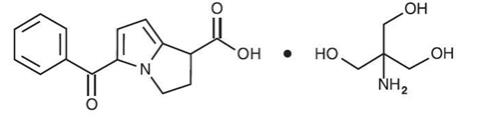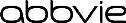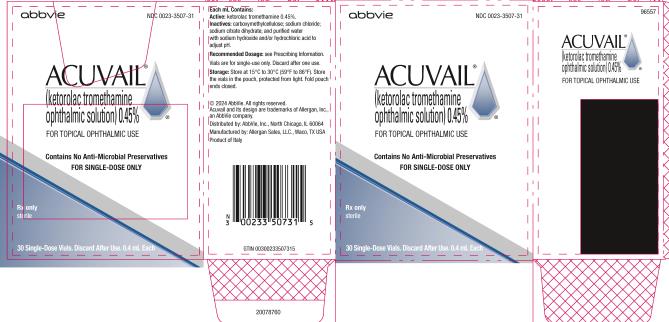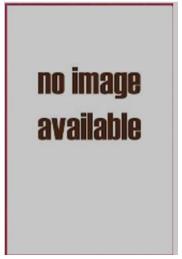 DRUG LABEL: ACUVAIL
NDC: 0023-3507 | Form: SOLUTION/ DROPS
Manufacturer: Allergan, Inc.
Category: prescription | Type: HUMAN PRESCRIPTION DRUG LABEL
Date: 20240531

ACTIVE INGREDIENTS: KETOROLAC TROMETHAMINE 4.5 mg/1 mL
INACTIVE INGREDIENTS: CARBOXYMETHYLCELLULOSE SODIUM, UNSPECIFIED; SODIUM CHLORIDE; TRISODIUM CITRATE DIHYDRATE; WATER; SODIUM HYDROXIDE; HYDROCHLORIC ACID

HIGHLIGHTS OF PRESCRIBING INFORMATION

These highlights do not include all the information needed to use ACUVAIL safely and effectively. See full prescribing information for ACUVAIL.
ACUVAIL® (ketorolac tromethamine ophthalmic solution) 0.45%, for topical ophthalmic use
Initial U.S. Approval: 1991

RECENT MAJOR CHANGES

Warnings and Precautions, Risk of Contamination (5.5) 5/2024

1 INDICATIONS AND USAGE

ACUVAIL is a nonsteroidal anti-inflammatory drug (NSAID) indicated for the treatment of pain and inflammation following cataract surgery. (1)

2 DOSAGE AND ADMINISTRATION

One drop of ACUVAIL should be applied to the affected eye twice daily beginning 1 day prior to cataract surgery, and continued through the first 2 weeks of the postoperative period. (2.1)

3 DOSAGE FORMS AND STRENGTHS

ACUVAIL ophthalmic solution containing 0.45% (4.5 mg/mL) ketorolac tromethamine in a single-dose vial. (3)

4 CONTRAINDICATIONS

Hypersensitivity to any component of this product. (4)

5 WARNINGS AND PRECAUTIONS

- Delayed healing (5.1)
- Cross-sensitivity or hypersensitivity (5.2)
- Increased bleeding time due to interference with thrombocyte aggregation (5.3)
- Corneal effects including keratitis (5.4)

6 ADVERSE REACTIONS

Most common adverse reactions occurring in 1% to 6% of patients were increased intraocular pressure, conjunctival hemorrhage, and vision blurred. (6.1)

To report SUSPECTED ADVERSE REACTIONS, contact AbbVie at 1-800-678-1605 or FDA at 1-800-FDA-1088 or www.fda.gov/medwatch.

FULL PRESCRIBING INFORMATION

1 INDICATIONS AND USAGE

ACUVAIL® is indicated for the treatment of pain and inflammation following cataract surgery.

2 DOSAGE AND ADMINISTRATION

2.1 Recommended Dosage

Apply one drop of ACUVAIL to the affected eye twice daily beginning 1 day prior to cataract surgery, continued on the day of surgery, and through the first 2 weeks of the postoperative period.

2.2 Use With Other Topical Ophthalmic Medications

ACUVAIL may be administered in conjunction with other topical ophthalmic medications such as alpha-agonists, beta-blockers, carbonic anhydrase inhibitors, cycloplegics, and mydriatics. Drops should be administered at least 5 minutes apart.

3 DOSAGE FORMS AND STRENGTHS

ACUVAIL (ketorolac tromethamine ophthalmic solution) is a sterile, clear, and colorless to pale yellow ophthalmic solution containing 0.45% (4.5 mg/mL) ketorolac tromethamine in a single-dose vial.

4 CONTRAINDICATIONS

ACUVAIL is contraindicated in patients with previously demonstrated hypersensitivity to any of the ingredients in the formulation [see Adverse Reactions (6.1)].

5 WARNINGS AND PRECAUTIONS

5.1 Delayed Healing

Topical nonsteroidal anti-inflammatory drugs (NSAIDs) may slow or delay healing. Topical corticosteroids are also known to slow or delay healing. Concomitant use of topical NSAIDs and topical steroids may increase the potential for healing problems.

5.2 Cross-Sensitivity or Hypersensitivity

There is the potential for cross-sensitivity to acetylsalicylic acid, phenylacetic acid derivatives, and other NSAIDs. There have been reports of bronchospasm or exacerbation of asthma associated with the use of ketorolac tromethamine ophthalmic solution in patients who either have a known hypersensitivity to aspirin/non-steroidal anti-inflammatory drugs, or a past medical history of asthma. Therefore, caution should be used when treating individuals who have previously exhibited sensitivities to these drugs.

5.3 Increased Bleeding Time

With some NSAIDs, there exists the potential for increased bleeding time due to interference with thrombocyte aggregation. There have been reports that ocularly applied nonsteroidal anti-inflammatory drugs may cause increased bleeding of ocular tissues (including hyphemas) in conjunction with ocular surgery.

It is recommended that ACUVAIL be used with caution in patients with known bleeding tendencies or who are receiving other medications, which may prolong bleeding time.

5.4 Corneal Effects

Use of topical NSAIDs may result in keratitis. In some susceptible patients, continued use of topical NSAIDs may result in epithelial breakdown, corneal thinning, corneal erosion, corneal ulceration, or corneal perforation. These events may be sight threatening. Patients with evidence of corneal epithelial breakdown should immediately discontinue use of topical NSAIDs and should be closely monitored for corneal health.

Postmarketing experience with topical NSAIDs suggests that patients with complicated ocular surgeries, corneal denervation, corneal epithelial defects, diabetes mellitus, ocular surface diseases (e.g., dry eye syndrome), rheumatoid arthritis, or repeat ocular surgeries within a short period of time may be at increased risk for corneal adverse events which may become sight threatening. Topical NSAIDs should be used with caution in these patients.

Postmarketing experience with topical NSAIDs also suggests that use more than 1 day prior to surgery or use beyond 14 days post-surgery may increase patient risk for the occurrence and severity of corneal adverse events.

5.5 Risk of Contamination

Avoid allowing the tip of the single-dose vial to contact the eye or surrounding structures because this could cause the tip to become contaminated by common bacteria known to cause ocular infections or cause injury to the eye. Serious damage to the eye and subsequent loss of vision may result from using contaminated solutions.

5.6 Contact Lens Wear

ACUVAIL should not be administered while wearing contact lenses.

6 ADVERSE REACTIONS

The following serious adverse reactions are described elsewhere in the labeling:

- Delayed Healing [see Warnings and Precautions (5.1)]
- Cross-Sensitivity or Hypersensitivity [see Warnings and Precautions (5.2)]
- Increased Bleeding Time [see Warnings and Precautions (5.3)]
- Corneal Effects [see Warnings and Precautions (5.4)]

6.1 Clinical Trials Experience

Because clinical trials are conducted under widely varying conditions, adverse reaction rates observed in the clinical trials of a drug cannot be directly compared to the rates in the clinical trials of another drug and may not reflect the rates observed in practice.

The most common adverse reactions were reported in 1% to 6% of patients and included increased intraocular pressure, conjunctival hyperemia and/or hemorrhage, corneal edema, ocular pain, headache, tearing and vision blurred. Some of these reactions may be the consequence of the cataract surgical procedure.

Other adverse reactions occurring during treatment with ketorolac tromethamine ophthalmic solutions included allergic reactions (including eye swelling, hyperemia, and pruritis).

6.2 Postmarketing Experience

The following adverse reactions have been identified during postapproval use of ketorolac tromethamine ophthalmic solutions in clinical practice. Because these reactions are reported voluntarily from a population of uncertain size, it is not always possible to reliably estimate their frequency or establish a causal relationship to the drug.

Eye Disorders: Corneal erosion, corneal perforation, corneal thinning and corneal melt, epithelial breakdown [see Warnings and Precautions (5.2, 5.4)], and ulcerative keratitis.

Respiratory, Thoracic and Mediastinal Disorders: Bronchospasm, exacerbation of asthma.

8 USE IN SPECIFIC POPULATIONS

8.1 Pregnancy

Risk Summary

There are no adequate and well-controlled studies with ACUVAIL in pregnant women. No evidence of teratogenicity has been observed in rats or rabbits with ACUVAIL at clinically relevant doses.

8.2 Lactation

Risk Summary

It is not known whether ketorolac when given topically is present in human milk. Because many drugs are excreted in human milk, caution should be exercised when ACUVAIL is administered to a nursing woman.

8.4 Pediatric Use

The safety and effectiveness of ACUVAIL have not been established in pediatric patients younger than 2 years old.

8.5 Geriatric Use

No overall differences in safety or effectiveness have been observed between elderly and other adult patients.

11 DESCRIPTION

ACUVAIL (ketorolac tromethamine ophthalmic solution) 0.45% is a member of the pyrrolo-pyrrole group of nonsteroidal anti-inflammatory drugs (NSAIDs) for topical ophthalmic use. Its chemical name is (±)-5-Benzoyl-2,3-dihydro-1H-pyrrolizine-1-carboxylic acid, compound with 2-amino-2-(hydroxymethyl)-1,3-propanediol (1:1), and its molecular weight is 376.40. Its molecular formula is C19H24N2O6. Its chemical structure is:

ACUVAIL solution is supplied as a sterile isotonic aqueous 0.45% solution, with a pH of approximately 6.8. ACUVAIL solution contains a racemic mixture of R-(+) and S-(-)- ketorolac tromethamine. Ketorolac tromethamine may exist in three crystal forms. All forms are equally soluble in water. The pKa of ketorolac is 3.5. This white to off-white crystalline substance discolors on prolonged exposure to light. The osmolality of ACUVAIL solution is approximately 285 mOsml/kg.

Each mL of ACUVAIL ophthalmic solution contains: Active: ketorolac tromethamine 0.45%. Inactives: carboxymethylcellulose sodium; sodium chloride; sodium citrate dihydrate; and purified water with sodium hydroxide and/or hydrochloric acid to adjust pH. ACUVAIL does not contain an anti-microbial preservative.

12 CLINICAL PHARMACOLOGY

12.1 Mechanism of Action

Ketorolac tromethamine is a nonsteroidal anti-inflammatory drug which, when administered systemically, has demonstrated analgesic, anti-inflammatory, and anti-pyretic activity. The mechanism of its action is thought to be due to its ability to inhibit prostaglandin biosynthesis.

12.3 Pharmacokinetics

Two drops of 0.5% ketorolac tromethamine ophthalmic solution instilled into the eyes of patients 12 hours and 1 hour prior to cataract extraction achieved a mean ketorolac concentration of 95 ng/mL in the aqueous humor of 8 of 9 eyes tested (range 40 to 170 ng/mL).

One drop of 0.5% ketorolac tromethamine ophthalmic solution was instilled into 1 eye and 1 drop of vehicle into the other eye three times daily in 26 healthy subjects. Five (5) of 26 subjects had detectable concentrations of ketorolac in their plasma (range 11 to 23 ng/mL) at Day 10 during topical ocular treatment. The range of concentrations following three times daily dosing of 0.5% ketorolac tromethamine ophthalmic solution are approximately 4 to 8% of the steady state mean minimum plasma concentration observed following four times daily oral administration of 10 mg ketorolac in humans (290 ± 70 ng/mL).

14 CLINICAL STUDIES

Two multicenter, randomized, double-masked, parallel group comparison studies including approximately 500 patients were conducted to evaluate the effects of ACUVAIL on anterior chamber cell and flare, and ocular pain relief following cataract extraction with posterior chamber intraocular lens (IOL) implantation. Results of these studies indicated that patients receiving ACUVAIL had a significantly higher incidence of clearing of anterior chamber inflammation 53% (167/318) versus patients receiving vehicle 26% (41/155) at day 14.

ACUVAIL was also significantly superior to vehicle in resolving ocular pain. On Day 1 post cataract surgery, 72% (233/322) of patients in the ACUVAIL group were pain free compared to 40% (62/156) of patients in the vehicle group.

Results from clinical studies indicate that ketorolac tromethamine has no significant effect upon intraocular pressure; however, changes in intraocular pressure may occur following cataract surgery.

16 HOW SUPPLIED/STORAGE AND HANDLING

ACUVAIL (ketorolac tromethamine ophthalmic solution) 0.45% is supplied as a sterile, clear, and colorless to pale yellow ophthalmic solution in clear, low density polyethylene (LDPE), single-dose vials packaged in 3 foil pouches, 10 vials per pouch:

30 Single-Dose Vials 0.4 mL each (Carton containing 3 pouches): NDC 0023-3507-31

Storage: Store at 15oC to 30ºC (59oF to 86ºF). Store the vials in the pouch, protected from light. Fold pouch ends closed. The solution from one individual single-dose vial is to be used immediately after opening. The remaining vial contents should be discarded.

17 PATIENT COUNSELING INFORMATION

Slow or Delayed Healing

Advise patients of the possibility that slow or delayed healing may occur while using nonsteroidal anti-inflammatory drugs (NSAIDs).

Avoiding Contamination of the Product

Instruct patients that the solution from one individual single-dose vial is to be used immediately after opening for administration to the affected eye. The remaining vial contents should be discarded.

Instruct patients to avoid allowing the tip of the single-dose vial to contact the eye or surrounding structures because this could cause the tip to become contaminated by common bacteria known to cause ocular infections or cause injury to the eye. Serious damage to the eye and subsequent loss of vision may result from using contaminated solutions.

Store the vials in the pouch, protected from light. Fold pouch ends closed.

Contact Lens Wear

Advise patients that ACUVAIL should not be administered while wearing contact lenses.

Intercurrent Ocular Conditions

Advise patients that if they develop an intercurrent ocular condition (e.g., trauma or infection) or have ocular surgery, they should immediately seek their physician’s advice concerning the continued use of ACUVAIL.

Concomitant Topical Ocular Therapy

Advise patients that if more than one topical ophthalmic medication is being used, the medicines should be administered at least 5 minutes apart.

Distributed by:
AbbVie Inc.
North Chicago, IL 60064

© 2024 AbbVie. All rights reserved.
ACUVAIL and its design are trademarks of Allergan, Inc., an AbbVie company.

V3.0USPI3507

PRINCIPAL DISPLAY PANEL

NDC 0023-3507-31

abbvie
ACUVAIL®
(ketorolac tromethamine
ophthalmic solution)0.45%
FOT TOPICAL OPHTHALMIC USE
Contains No Anti-Microbial Preservatives
FOR SINGLE-DOSE ONLY
Rx Only
sterile
30 Single-Dose Vials. Discard After Use. 0.4mL Each

PRINCIPAL DISPLAY PANEL

NDC 0023-3507-30